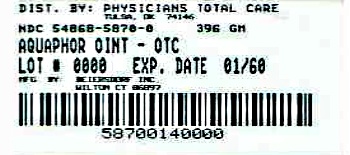 DRUG LABEL: Aquaphor
NDC: 54868-5870 | Form: OINTMENT
Manufacturer: Physicians Total Care, Inc.
Category: otc | Type: HUMAN OTC DRUG LABEL
Date: 20120521

ACTIVE INGREDIENTS: Petrolatum 41 g/100 g
INACTIVE INGREDIENTS: MINERAL OIL; CERESIN; LANOLIN ALCOHOLS

ACTIVE INGREDIENTS

Petrolatum 41%

PURPOSE

Skin protectant ointment

INDICATIONS AND USAGE

Uses
• temporarily protects minor: • cuts • scrapes • burns
• temporarily protects and helps relieve chapped or cracked
skin and lips
• helps protect from the drying effects of wind and
cold weather

Directions Apply as needed

WARNINGS

For external use only

When using this product do not get into eyes

Do not use on • deep or puncture wounds • animal bites
• serious burns

Stop use and ask a doctor if • condition worsens
• symptoms last more than 7 days or clear up and occur
again within a few days

Keep out of reach of children. If swallowed, get medical
help or contact a Poison Control Center right away.

INACTIVE INGREDIENTS

Mineral Oil, Ceresin, Lanolin Alcohol

QUESTIONS

Questions or comments? 1-800-227-4703

DIRECTIONS

For the pharmacist: Aquaphor provides an ideal base for
compounding smooth, stable emulsions. It is highly miscible
with aqueous solutions and oil based substances.

PRINCIPAL DISPLAY PANEL

Aquaphor
OINTMENT

Skin Protectant

Ideal for Compounding

Dermatologist Recommended

SEVERELY DR Y SKIN TREATMENT
Clinically proven to restore smooth, healthy skin

NET WT
14 oz
396 g

Additional barcode labeling by:
Physicians Total Care, Inc.
Tulsa, Oklahoma 74146